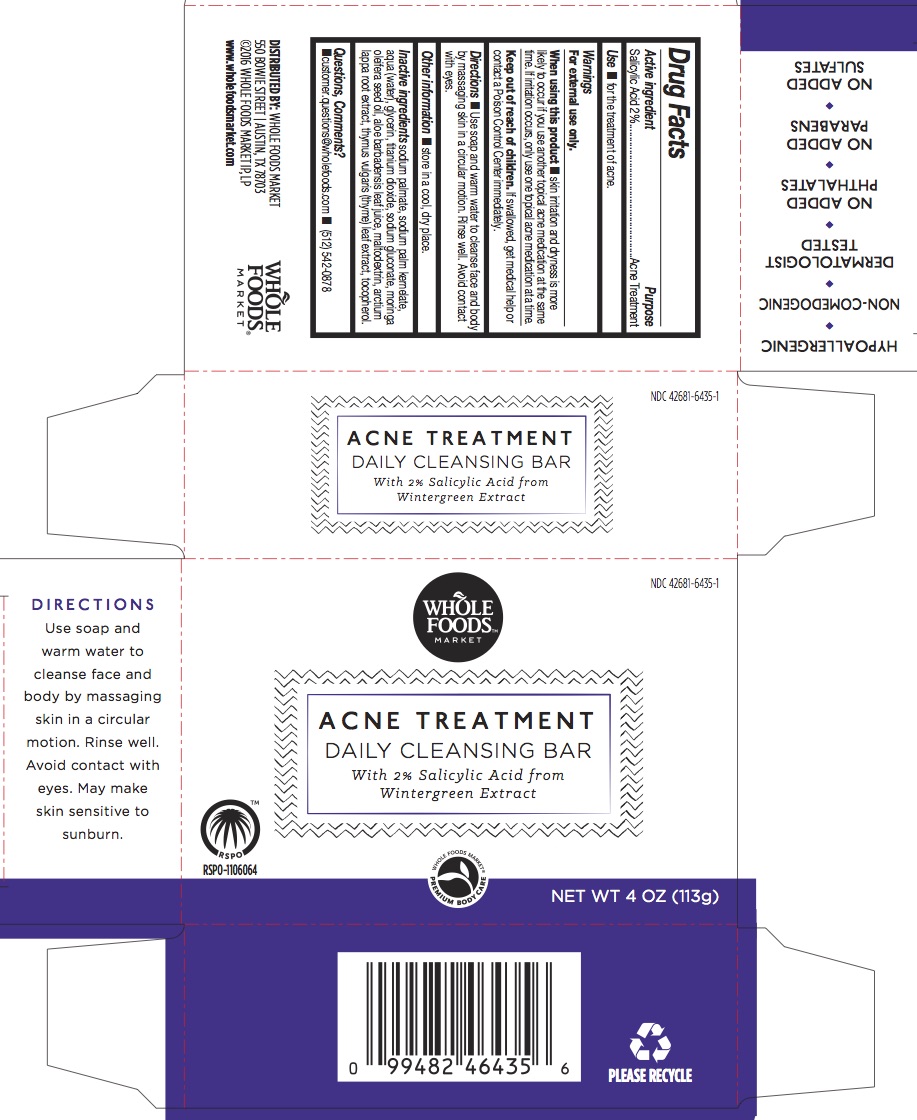 DRUG LABEL: ACNE TREATMENT DAILY CLEANSING BAR
NDC: 42681-6435 | Form: SOAP
Manufacturer: Whole Foods Market
Category: otc | Type: HUMAN OTC DRUG LABEL
Date: 20170131

ACTIVE INGREDIENTS: SALICYLIC ACID 2 g/100 g
INACTIVE INGREDIENTS: SODIUM GLUCONATE; MORINGA OLEIFERA SEED OIL; TOCOPHEROL; WATER; SODIUM PALMATE; SODIUM PALM KERNELATE; GLYCERIN; TITANIUM DIOXIDE; MALTODEXTRIN; ALOE; THYMUS VULGARIS LEAF; ARCTIUM LAPPA ROOT OIL

ACNE TREATMENT DAILY CLEANSING BAR

Active Ingredient

Salicylic Acid 2%

Purpose

Acne Treatment

Use

For for the treatment of acne

Warnings

For external use only

- Keep out of the reach of children.
- If swallowed, get medical help or contact a Poison Control Center immediately.

Directions

- Use soap and warm water to cleanse face and body by massaging skin in a circular motion. Rinse well. Avoid contact with eyes.

When using this product skin irritation and dryness are more likely to occur if you use another topical acne medication at the same time. If irritation occurs, only use one topical acne medication at a time.

INACTIVE INGREDIENT

Sodium Palmate, Sodium Palm Kernelate, Water, Glycerin, Salicylic Acid, Titanium Dioxide, Moringa Oleifera Seed Oil, Maltodextrin, Aloe Barbadensis Leaf Juice, Thymus Vulgaris (Thyme) Leaf Extract, Arctium Lappa Root Extract, Tocopherol

Questions, Comments?

■ customer.questions@wholefoods.com ■ (512) 542-0878